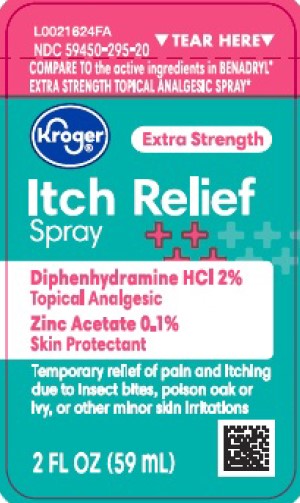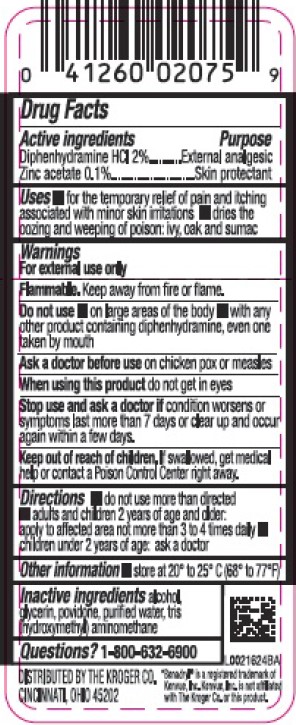 DRUG LABEL: Itch Relief
NDC: 59450-295 | Form: SPRAY
Manufacturer: The Kroger Co.
Category: otc | Type: HUMAN OTC DRUG LABEL
Date: 20260227

ACTIVE INGREDIENTS: ZINC ACETATE 1 mg/1 mL; DIPHENHYDRAMINE HYDROCHLORIDE 20 mg/1 mL
INACTIVE INGREDIENTS: GLYCERIN; POVIDONE; TROMETHAMINE; ALCOHOL; WATER

Kroger 295.000/295AA-AB
Itch Relief Spray

Active ingredients

Diphenhydramine HCl 2%

Zinc acetate 0.1%

Purpose

External analgesic

Skin protectant

Uses

- for the temporary relief of pain and itching associated with minor skin irritations
- dries the oozing and weeping of poison: ivy, oak and sumac

Warnings

For external use only

Flammable. Keep away from fire or flame.

Do not use

- on large areas of the body
- with any other product containing diphenhydramine, even one taken by mouth

Ask a doctor before use

on chicken pox or measles

When using this product

do not get into eyes

Stop use and ask a doctor if

condition worsens or symptoms last more than 7 days or clear up and occur again within a few days.

Keep out of reach of children.

If swallowed, get medical help or contact a Poison Control Center right away.

Directions

- do not use more than directed
- adults and children 2 years of age and older: apply to affected area not more than 3 to 4 times daily
- children under 2 years of age: ask a doctor

Other

- store at 20º to 25º C (68º to 70ºF)

Inactive ingredients

alcohol, glycerin, povidone, purified water, tris (hydroxymethyl) aminomethane

Questions?

1-800-632-6900

Adverse reaction

DISTRIBUTED BY THE KROGER CO.CINCINNATI, OHIO 45202

Disclaimer

Benadryl®is a registered trademark of Kenvue, Inc. Kenvue, Inc. is not affiliated with The Kroger Co. or this product.

Principal display panel

TEAR HERE

NDC 59450-295-20

COMPARE TO the active ingredients in BENADRYL®EXTRA STRENGTH TOPCICAL ANALGESIC SPRAY*

Kroger®

Extra Strength

Itch Relief Spray

Diphenhydramine HCI 2%

Topical Analgesic

Zinc Acetone 0.1%

Skin Protectant

Temporary relief of pain and itching due to insect bites, poison ivy or oak, or other minor skin irritations

2 FL OZ (59 mL)